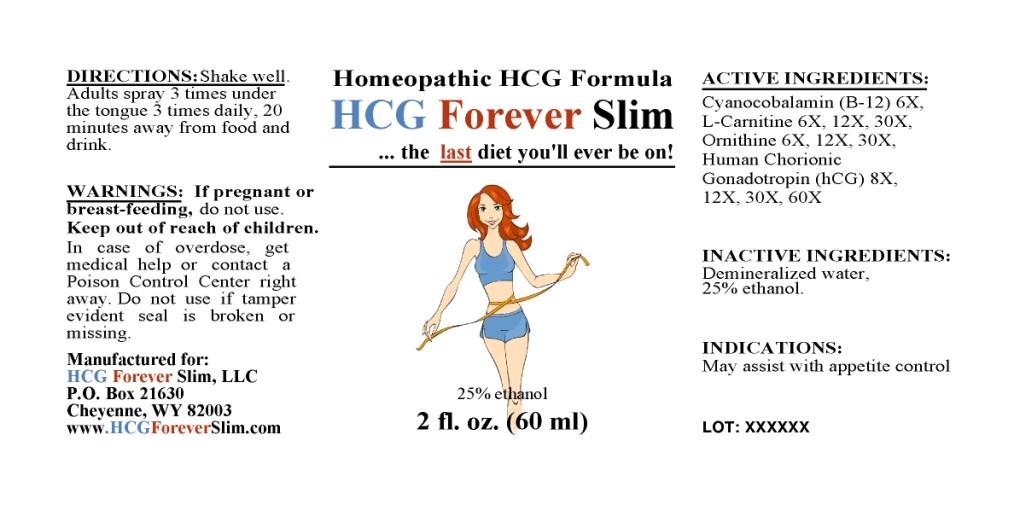 DRUG LABEL: Homeopathic HCG Formula
NDC: 57520-0608 | Form: LIQUID
Manufacturer: Apotheca Company
Category: homeopathic | Type: HUMAN OTC DRUG LABEL
Date: 20110217

ACTIVE INGREDIENTS: CYANOCOBALAMIN 6 [hp_X]/1 mL; LEVOCARNITINE 30 [hp_X]/1 mL; ORNITHINE 30 [hp_X]/1 mL; HUMAN CHORIONIC GONADOTROPIN 60 [hp_X]/1 mL
INACTIVE INGREDIENTS: WATER; ALCOHOL

Homeopathic HCG Formula

ACTIVE INGREDIENT

ACTIVE INGREDIENTS: Cyanocobalamin (B-12) 6X, L-Carnitine 6X, 12X, 30X, Ornithine 6X, 12X, 30X, Human chorionic gonadotropin (HCG) 8X, 12X, 30X, 60X.

PURPOSE

INDICATIONS: May assist with appetite control.

WARNINGS

WARNINGS: If pregnant or breast-feeding, do not use.

Keep out of reach of children. In case of overdose, get medical help or contact a Poison Control Center right away.

Do not use if tamper evident seal is broken or missing.

DOSAGE AND ADMINISTRATION

DIRECTIONS: Shake well. Adults spray 3 times under the tongue 3 times daily, 20 minutes away from food and drink.

INACTIVE INGREDIENTS: Demineralized water, 25% Ethanol.

KEEP OUT OF REACH OF CHILDREN. In case of overdose, get medical help or contact a Poison Control Center right away.

INDICATIONS: May assist with appetite control.

QUESTIONS

Manufactured for:

HCG Forever Slim, LLC

P.O. Box 21630

Cheyenne, WY 82003

www.HCGForeverSlim.com

PACKAGE LABEL

Homeopathic HCG Formula

HCG Forever Slim

the last diet you'll ever be on!

2 fl. oz. (60 ml)